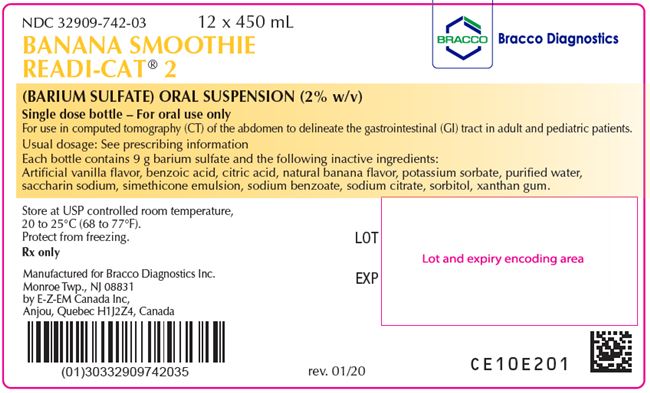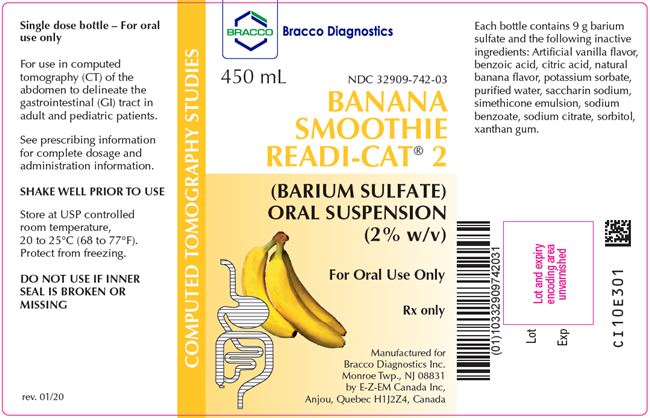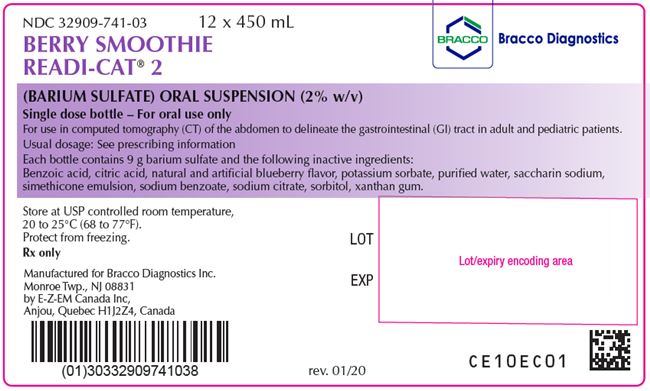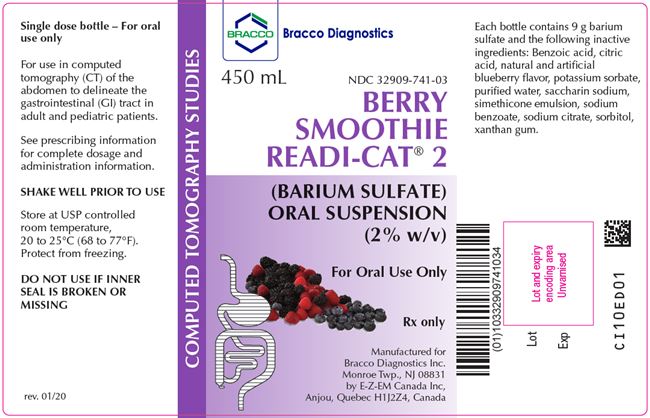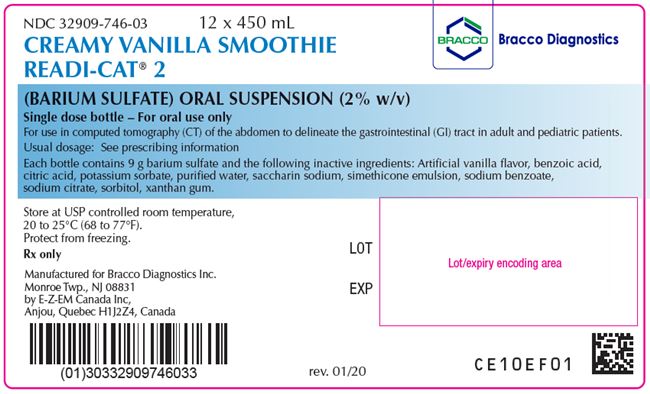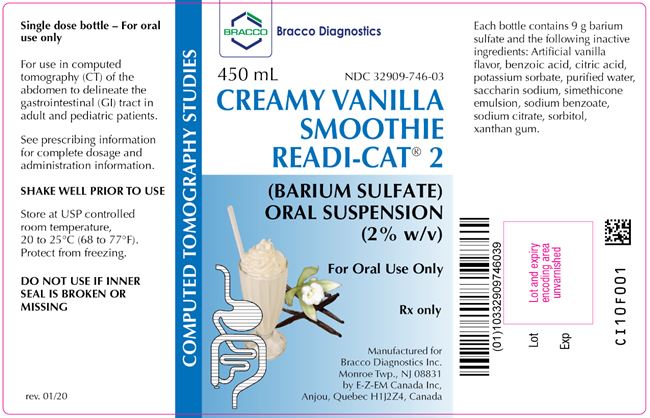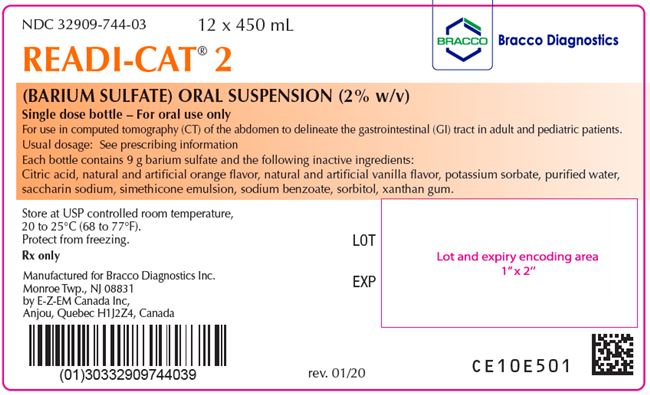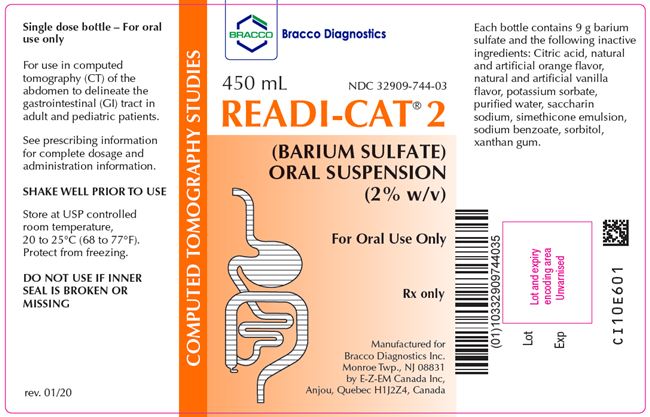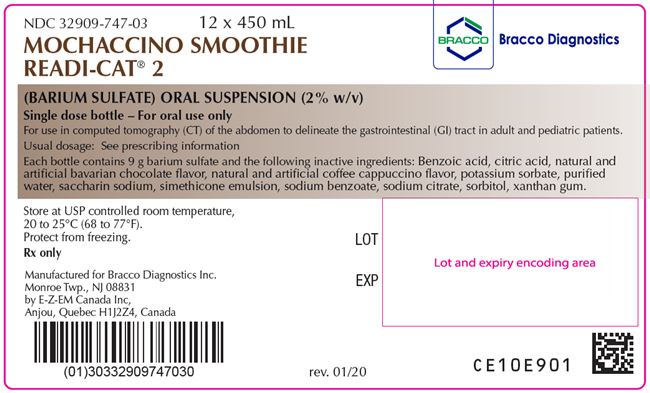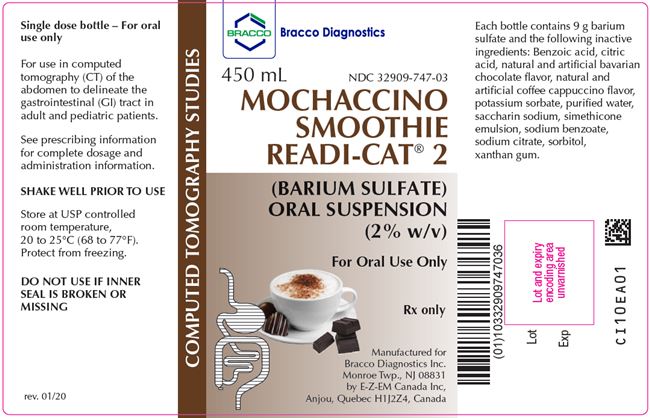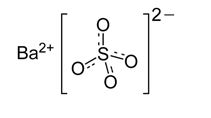 DRUG LABEL: Readi-Cat 2
NDC: 32909-724 | Form: SUSPENSION
Manufacturer: E-Z-EM Canada Inc
Category: prescription | Type: HUMAN PRESCRIPTION DRUG LABEL
Date: 20201009

ACTIVE INGREDIENTS: Barium Sulfate 20 mg/1 mL
INACTIVE INGREDIENTS: anhydrous citric acid; dimethicone 350; dimethicone 1000; potassium sorbate; silicon dioxide; sodium benzoate; sorbitol; water; xanthan gum; saccharin sodium

HIGHLIGHTS OF PRESCRIBING INFORMATION

These highlights do not include all the information needed to use READI-CAT 2 and READI-CAT 2 SMOOTHIE products safely and effectively. See full prescribing information for
READI-CAT 2 (barium sulfate) oral suspension
READI-CAT 2 SMOOTHIE (barium sulfate) oral suspension
Initial U.S. Approval: 2016

RECENT MAJOR CHANGES

Warning and Precautions (5.6) | 2/2017

1 INDICATIONS AND USAGE

READI-CAT 2 and READI-CAT 2 SMOOTHIE are radiographic contrast agents, indicated for use in computed tomography (CT) of the abdomen to delineate the gastrointestinal (GI) tract in adult and pediatric patients (1)

2 DOSAGE AND ADMINISTRATION

For oral use only:

- Adults and pediatric patients 12 years and older: 450 mL to 900 mL (9 g to 18 g of barium sulfate, respectively) (2.1)
- Patients younger than 12 years of age: scale down dose based on relative GI volume (2.1)

3 DOSAGE FORMS AND STRENGTHS

- Oral Suspension: 9 grams barium sulfate (2% w/v) supplied in a single dose HDPE plastic bottle (3)

4 CONTRAINDICATIONS

- Known or suspected perforation of the GI tract (4)
- Known obstruction of the GI tract (4)
- Conditions associated with high risk of GI perforation or aspiration (4)
- Known hypersensitivity to barium sulfate or any of the excipients of READI-CAT 2 products (4)

5 WARNINGS AND PRECAUTIONS

- Hypersensitivity reactions: Emergency equipment and trained personnel should be immediately available (5.1)
- Intra-abdominal leakage: May occur in conditions such as GI fistula, ulcer, inflammatory bowel disease, appendicitis or diverticulitis, severe stenosis or obstructing lesions of the GI tract (5.2)
- Delayed GI transit and obstruction: Patients should maintain adequate hydration in days following a barium sulfate procedure to avoid obstruction or impaction (5.3)
- Aspiration: Caution is recommended in patients with history of food aspiration and in patients with known swallowing disorders (5.4)

6 ADVERSE REACTIONS

Common adverse reactions include nausea, vomiting, diarrhea and abdominal cramping (6)

To report SUSPECTED ADVERSE REACTIONS, contact Bracco Diagnostics Inc at 1-800-257-5181 or FDA at 1-800-FDA-1088 or www.fda.gov/medwatch.

FULL PRESCRIBING INFORMATION

1 INDICATIONS AND USAGE

READI-CAT 2 and READI-CAT 2 SMOOTHIES are indicated for use in computed tomography (CT) of the abdomen to delineate the gastrointestinal (GI) tract in adult and pediatric patients.

2 DOSAGE AND ADMINISTRATION

2.1 Recommended Dosage

Base dosing on individual needs and procedure to be performed.

- Adult and pediatric patients 12 years and older: 450 mL to 900 mL (9 g to 18 g of barium sulfate)
- Patients younger than 12 years of age: adjust dose based on relative GI volume

2.2 Administration Instructions

- For oral use only
- Shake bottle vigorously for 30 seconds prior to oral administration
- Administer undiluted prior to scan
- Discard any unused suspension
- Advise patients to hydrate following the barium sulfate procedure

3 DOSAGE FORMS AND STRENGTHS

Oral suspension: 9 grams of barium sulfate supplied as a suspension (2% w/v) in a single-dose HDPE plastic bottle.

4 CONTRAINDICATIONS

READI-CAT 2 products are contraindicated in patients:

- with known or suspected perforation of the GI tract
- with known obstruction of the GI tract
- at high risk of GI perforation such as those with a recent prior GI perforation, acute GI hemorrhage or ischemia, toxic megacolon, severe ileus, post GI surgery or biopsy, acute GI injury or burn, or recent radiotherapy to pelvis
- at high risk of aspiration such as those with prior aspiration, tracheo-esophageal fistula, or obtundation
- known severe hypersensitivity to barium sulfate or any of the excipients of READI-CAT 2 or READI-CAT 2 SMOOTHIES

5 WARNINGS AND PRECAUTIONS

5.1 Hypersensitivity Reactions

Barium sulfate preparations contain a number of excipients, including natural and artificial flavors and may induce serious hypersensitivity reactions. The manifestations include hypotension, bronchospasm and other respiratory impairments, dermal reactions including rashes, urticaria, and itching. A history of bronchial asthma, atopy, or a previous reaction to a contrast agent may increase the risk for hypersensitivity reactions. Emergency equipment and trained personnel should be immediately available for treatment of a hypersensitivity reaction.

5.2 Intra-abdominal Barium Leakage

The use of READI-CAT 2 products is contraindicated in patients at high risk of perforation of the GI tract [see Contraindications (4)]. Administration of READI-CAT 2 products may result in leakage of barium from the GI tract in the presence of conditions such as carcinomas, GI fistula, inflammatory bowel disease, gastric or duodenal ulcer, appendicitis, or diverticulitis, and in patients with a severe stenosis at any level of the GI tract, especially if it is distal to the stomach. The barium leakage has been associated with peritonitis and granuloma formation.

5.3 Delayed Gastrointestinal Transit and Obstruction

Orally administered barium sulfate may accumulate proximal to a constricting lesion of the colon, causing obstruction or impaction with development of baroliths (inspissated barium associated with feces) and may lead to abdominal pain, appendicitis, bowel obstruction, or rarely perforation. Patients with the following conditions are at higher risk for developing obstruction or baroliths: severe stenosis at any level of the GI tract, impaired GI motility, electrolyte imbalance, dehydration, on a low residue diet, taking medications that delay GI motility, and constipation, pediatric patients with cystic fibrosis or Hirschsprung disease, and the elderly [see Use in Specific Populations (8.4, 8.5)]. To reduce the risk of delayed GI transit and obstruction, patients should maintain adequate hydration following a barium sulfate procedure.

5.4 Aspiration Pneumonitis

The use of READI-CAT 2 products is contraindicated in patients at high risk of aspiration [see Contraindications (4)]. Oral administration of barium is associated with aspiration pneumonitis, especially in patients with a history of food aspiration or with compromised swallowing mechanism. Vomiting following oral administration of barium sulfate may lead to aspiration pneumonitis. In patients at risk for aspiration, begin the procedure with a small ingested volume of READI-CAT 2 products. Discontinue administration of READI-CAT 2 products immediately if aspiration is suspected.

5.5 Systemic Embolization

Barium sulfate products may occasionally intravasate into the venous drainage of the large bowel and enter the circulation as a "barium embolus" leading to potentially fatal complications which include systemic and pulmonary embolism, disseminated intravascular coagulation, septicemia and prolonged severe hypotension. Although this complication is exceedingly uncommon after oral administration of barium sulfate suspension, monitor patients for potential intravasation when administering barium sulfate.

5.6 Risk with Hereditary Fructose Intolerance

READI-CAT 2 contains sorbitol which may cause severe reactions if ingested by patients with hereditary fructose intolerance, such as: vomiting, hypoglycemia, jaundice, hemorrhage, hepatomegaly, hyperuricemia, and kidney failure. Before administration of READI-CAT 2 assess patients for a history of hereditary fructose intolerance and avoid use in these patients.

6 ADVERSE REACTIONS

The following adverse reactions have been identified from spontaneous reporting or clinical studies of barium sulfate administered orally. Because the reactions are reported voluntarily from a population of uncertain size, it is not always possible to reliably estimate their frequency or to establish a causal relationship to drug exposure:

- Nausea, vomiting, diarrhea and abdominal cramping
- Serious adverse reactions and fatalities include aspiration pneumonitis, barium sulfate impaction, intestinal perforation with consequent peritonitis and granuloma formation, vasovagal and syncopal episodes

8 USES IN SPECIFIC POPULATIONS

8.1 Pregnancy

Risk Summary
READI-CAT 2 products are not absorbed systemically following oral administration, and maternal use is not expected to result in fetal exposure to the drug.

8.2 Lactation

Risk Summary
READI-CAT 2 products are not absorbed systemically by the mother following oral administration, and breastfeeding is not expected to result in exposure of the infant to READI-CAT 2.

8.4 Pediatric Use

The efficacy of READI-CAT 2 in pediatric patients of all groups is based on successful opacification of the GI tract during radiographic procedures [see Clinical Pharmacology (12.1)].

READI-CAT 2 is contraindicated in pediatric patients with tracheo-esophageal fistula [see Contraindications (4)].

Pediatric patients with a history of asthma or food allergies may be at increased risk for development of hypersensitivity reactions [see Warnings and Precautions (5.1)]. Pediatric patients with cystic fibrosis or Hirschsprung disease should be monitored for bowel obstruction after use [see Warnings and Precautions (5.3)].

8.5 Geriatric Use

Clinical studies of READI-CAT 2 products do not include sufficient numbers of subjects aged 65 and over to determine whether they respond differently from younger subjects. Other reported clinical experience has not identified differences in responses between the elderly and younger patients. In general, dose selection for an elderly patient should be cautious, usually starting at the low end of the dosing range, reflecting the greater frequency of decreased hepatic, renal, or cardiac function, and of concomitant disease or other drug therapy.

11 DESCRIPTION

READI-CAT 2 and READI-CAT 2 SMOOTHIE (barium sulfate) are radiographic contrast agents supplied as a suspension (2% w/v) for oral administration. The active ingredient barium sulfate is designated chemically as BaSO4 with a molecular weight of 233.4 g/mol, a density of 4.5 g/cm^3, and the following chemical structure:

READI-CAT 2 products contain excipients including: benzoic acid, citric acid, potassium sorbate, saccharin sodium, simethicone emulsion, sodium benzoate, sodium citrate, sorbitol solution, xanthan gum, and purified water.

READI-CAT 2 products also contain natural and artificial flavorings including: banana, blueberry, orange, vanilla, chocolate, and coffee flavors.

12 CLINICAL PHARMACOLOGY

12.1 Mechanism of Action

Due to its high atomic number, barium (the active ingredient in READI-CAT 2 products) is opaque to x-rays and therefore acts as a positive contrast agent for radiographic studies.

12.3 Pharmacokinetics

Under physiological conditions, barium sulfate passes through the GI tract in an unchanged form and is absorbed only in pharmacologically insignificant amounts.

13 NONCLINICAL TOXICOLOGY

13.1 Carcinogenesis, Mutagenesis, Impairment of Fertility

No animal studies have been performed to evaluate the carcinogenic potential of barium sulfate or potential effects on fertility.

16 HOW SUPPLIED/STORAGE AND HANDLING

16.1 How Supplied

READI-CAT 2 and READI-CAT 2 SMOOTHIES (barium sulfate) are supplied as suspensions (2 % w/v) in a unit dose in a single-dose HDPE plastic bottle containing 9 grams of barium sulfate in 450 mL.

READI-CAT 2 products are provided in the following flavors as:

READI-CAT 2: (Orange): 12 x 450 mL bottles (NDC 32909-744-03)
READI-CAT 2 SMOOTHIE (Banana): 12 x 450 mL bottles (NDC 32909-742-03)
READI-CAT 2 SMOOTHIE (Berry): 12 x 450 mL bottles (NDC 32909-741-03)
READI-CAT 2 SMOOTHIE (Creamy Vanilla): 12 x 450 mL bottles (NDC 32909-746-03)
READI-CAT 2 SMOOTHIE (Mochaccino): 12 x 450 mL bottles (NDC 32909-747-03)

16.2 Storage and Handling

Store at USP controlled room temperature, 20 to 25°C (68 to 77° F)

17 PATIENT COUNSELING INFORMATION

After administration advise patients to:

- Maintain adequate hydration
- Seek medical attention for worsening of constipation or slow gastrointestinal passage
- Seek medical attention for any delayed onset of hypersensitivity: rash, urticaria, or respiratory difficulty.

Manufactured by
EZEM Canada Inc
Anjou (Quebec) Canada H1J 2Z4

For
Bracco Diagnostics Inc.
Monroe Township, NJ 08831

Revised January 2020

CL10E801

PACKAGE LABEL

Readi–Cat® 2 Barium Sulfate Suspension Labels
NDC: 32909-744-03

PACKAGE LABEL

Readi–Cat® 2 Barium Sulfate Suspension Labels — Banana Smoothie
NDC: 32909-742-03

PACKAGE LABEL

Readi–Cat® 2 Barium Sulfate Suspension Labels
NDC: 32909-741-03

PACKAGE LABEL

Readi–Cat® 2 Barium Sulfate Suspension Labels
NDC: 32909-747-03

PACKAGE LABEL

Readi–Cat® 2 Barium Sulfate Suspension Labels
NDC: 32909-746-03